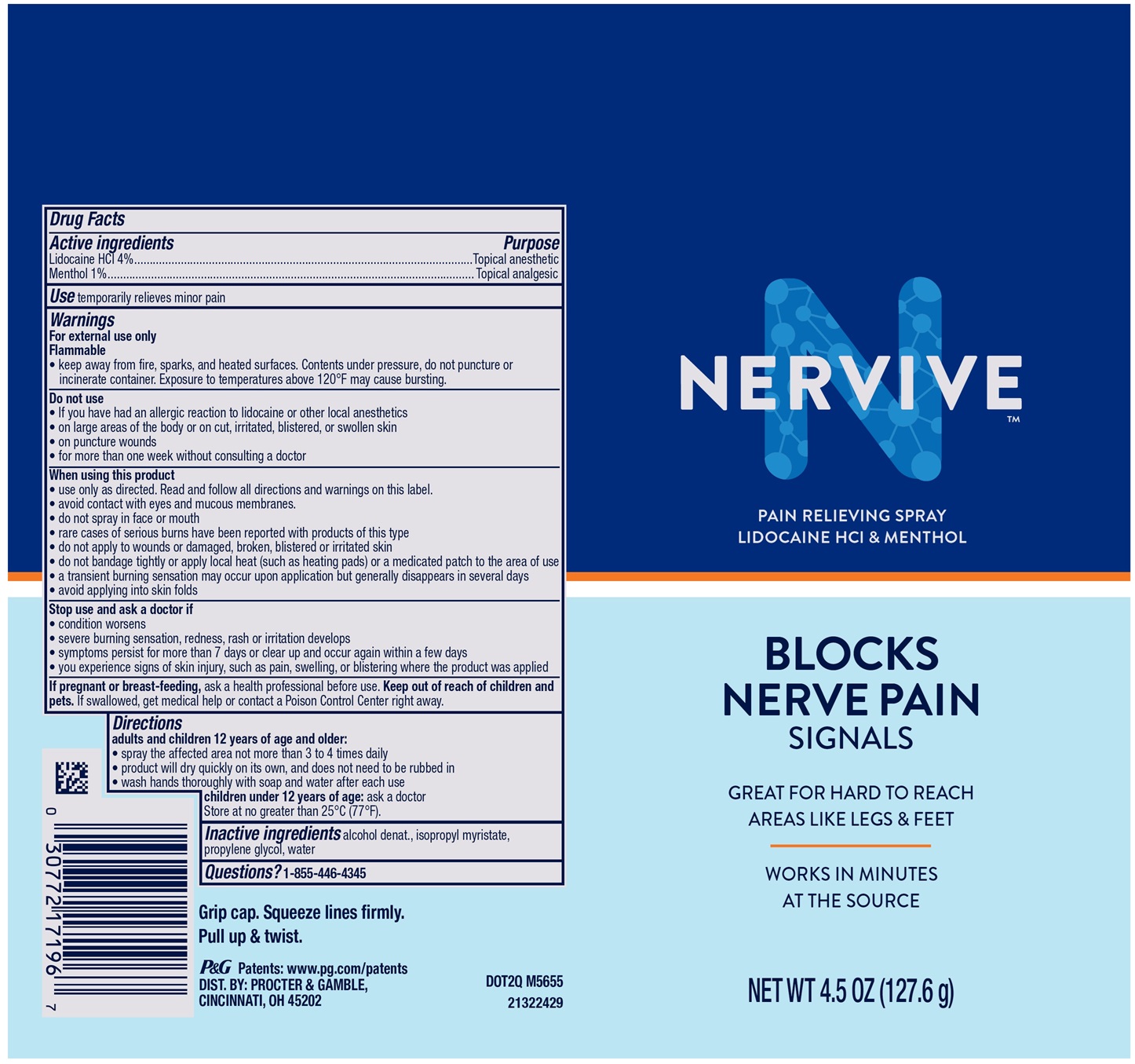 DRUG LABEL: Nervive Pain Relieving
NDC: 84126-319 | Form: SPRAY
Manufacturer: The Procter & Gamble Manufacturing Company
Category: otc | Type: HUMAN OTC DRUG LABEL
Date: 20250415

ACTIVE INGREDIENTS: LIDOCAINE HYDROCHLORIDE 4 g/100 g; MENTHOL 1 g/100 g
INACTIVE INGREDIENTS: ALCOHOL; WATER; ISOPROPYL MYRISTATE; PROPYLENE GLYCOL

NERVIVE™ PAIN RELIEVING SPRAY

Drug Facts

Active ingredients

Lidocaine HCl 4%

Menthol 1%

Active ingredients Purpose

Topical anesthetic

Topical analgesic

Use

temporarily relieves minor pain

Warnings

For external use only

Flammable

- keep away from fire, sparks, and heated surfaces. Contents under pressure, do not puncture or incinerate container. Exposure to temperatures above 120°F may cause bursting.

Do not use

- If you have had an allergic reaction to lidocaine or other local anesthetics
- on large areas of the body or on cut, irritated, blistered, or swollen skin
- on puncture wounds
- for more than one week without consulting a doctor

When using this product

- use only as directed. Read and follow all directions and warnings on this label.
- avoid contact with eyes and mucous membranes.
- do not spray in face or mouth
- rare cases of serious burns have been reported with products of this type
- do not apply to wounds or damaged, broken, blistered or irritated skin
- do not bandage tightly or apply local heat (such as heating pads) or a medicated patch to the area of use
- a transient burning sensation may occur upon application but generally disappears in several days
- avoid applying into skin folds

Stop use and ask a doctor if

- condition worsens
- severe burning sensation, redness, rash or irritation develops
- symptoms persist for more than 7 days or clear up and occur again within a few days
- you experience signs of skin injury, such as pain, swelling, or blistering where the product was applied

If pregnant or breast-feeding,

ask a health professional before use.

Keep out of reach of children and pets.

OVERDOSAGE

If swallowed, get medical help or contact a Poison Control Center right away.

Directions

adults and children over 12 years of age and older:

- spray the affected area not more than 3 to 4 times daily
- product will dry quickly on its own, and does not need to be rubbed in
- wash hands thoroughly with soap and water after each use

children under 12 years of age: ask a doctor

Store at no greater than 25°C (77°F).

Inactive ingredients

alcohol denat., isopropyl myristate, propylene glycol, water

Questions?

1-855-446-4345

Grip cap. Squeeze lines firmly.

Pull up & twist.

DIST. BY: PROCTER & GAMBLE, CINCINNATI, OH 45202

PRINCIPAL DISPLAY PANEL - 4.5 OZ

NERVIVE™

PAIN RELIEVING SPRAY

LIDOCAINE HCl & MENTHOL

BLOCKS NERVE PAIN

SIGNALS

GREAT FOR HARD TO REACH AREAS LIKE LEGS & FEET

WORKS IN MINUTES AT THE SOURCE

NET WT 4.5 OZ (127.6 g)